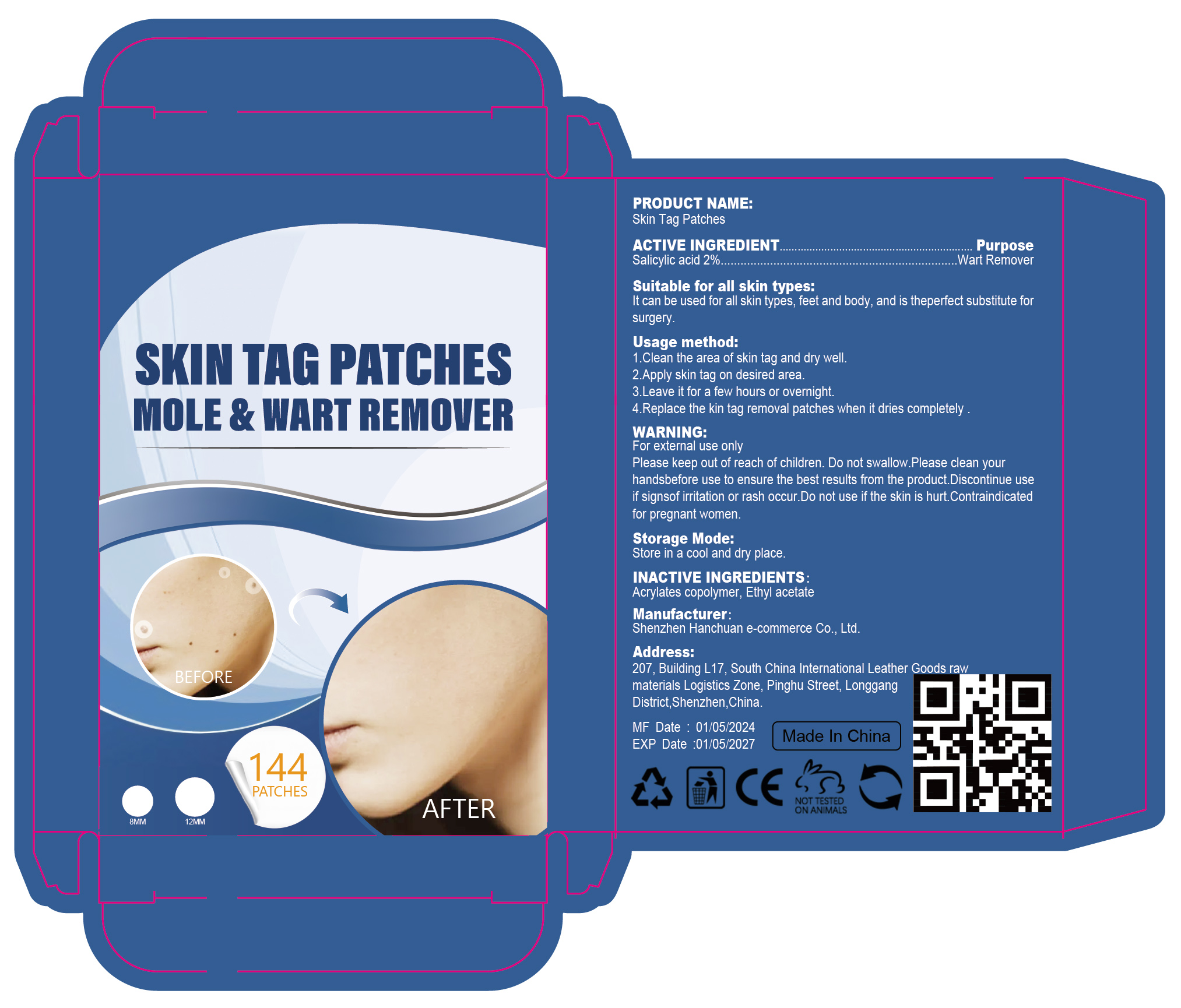 DRUG LABEL: Skin Tag Patches
NDC: 84302-007 | Form: PATCH
Manufacturer: Shenzhen Hanchuan e-commerce Co., Ltd
Category: otc | Type: HUMAN OTC DRUG LABEL
Date: 20240517

ACTIVE INGREDIENTS: SALICYLIC ACID 2 g/100 1
INACTIVE INGREDIENTS: BUTYL ACRYLATE/METHYL METHACRYLATE/METHACRYLIC ACID COPOLYMER (18000 MW); ETHYL ACETATE

Skin Tag Patches

ACTIVE INGREDIENT

Salicylic acid 2%

PURPOSE

Wart Remover

Please keep out of reach of children.

INDICATIONS AND USAGE

lt can be used for all skin types, feet and body, and is theperfect substitute for
surgery.

WARNINGS

For external use only
Please keep out of reach of children. Do not swallow.Please clean yourhandsbefore use to ensure the best results from the product.Discontinue useif signsof irritation or rash occur.Do not use if the skin is hurt.Contraindicatedfor pregnant women.

DOSAGE AND ADMINISTRATION

1.Clean the area of skin tag and dry well.
2.Apply skin tag on desired area
3.Leave it for a few hours or overnight.
4Replace the kin tag removal patches when it dries completely

STORAGE AND HANDLING

Store in a cool and dry place.

INACTIVE INGREDIENT

Acrylates copolymer
Ethyl acetate